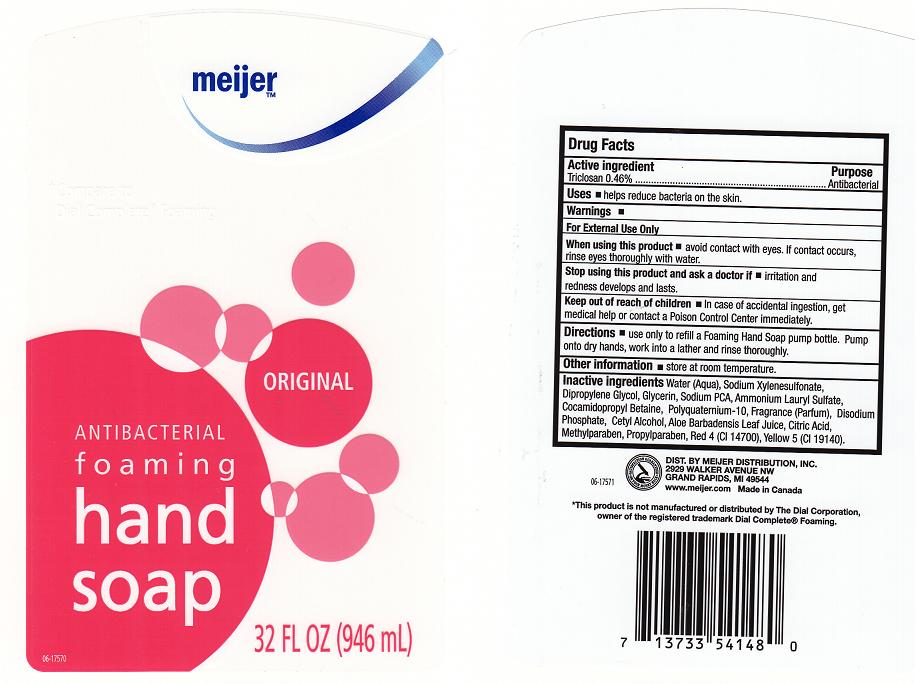 DRUG LABEL: ANTIBACTERIAL FOAMING
NDC: 41250-177 | Form: LIQUID
Manufacturer: MEIJER DISTRIBUTION INC
Category: otc | Type: HUMAN OTC DRUG LABEL
Date: 20111118

ACTIVE INGREDIENTS: TRICLOSAN 0.46 mL/100 mL
INACTIVE INGREDIENTS: WATER; SODIUM XYLENESULFONATE; DIPROPYLENE GLYCOL; GLYCERIN; SODIUM PYRROLIDONE CARBOXYLATE; AMMONIUM LAURYL SULFATE; COCAMIDOPROPYL BETAINE; POLYQUATERNIUM-10 (400 CPS AT 2%); SODIUM PHOSPHATE; C12-16 ALCOHOLS; ALOE VERA LEAF; CITRIC ACID MONOHYDRATE; METHYLPARABEN; PROPYLPARABEN; FD&C RED NO. 4; FD&C YELLOW NO. 5

DRUG FACTS

ACTIVE INGREDIENT

TRICLOSAN 0.46%

PURPOSE

ANTIBACTERIAL

USES

HELPS REDUCES BACTERIA ON THE SKIN

WARNINGS

FOR EXTERNAL USE ONLY

WHEN USING THIS PRODUCT

AVOID CONTACT WITH EYES. IF CONTACT OCCURS, RINSE THOROUGHLY WITH WATER.

STOP USING THIS PRODUCT AND ASK DOCTOR

IF IRRITATION AND REDNESS DEVELOP AND LAST.

KEEP OUT OF REACH OF CHILDREN

IN CASE OF ACCIDENTAL INGESTION, GET MEDICAL HELP OR CONTACT POISON CONTROL CENTER IMMEDIATELY.

DIRECTIONS

PUMP ONTO DRY HANDS. WORK INTO A LATHER AND RINSE THOROUGHLY.

OTHER INFORMATION

STORE AT ROOM TEMPERATURE.

INACTIVE INGREDIENTS

WATER (AQUA), SODIUM XYLENESULFONATE, DIPROPYLENE GLYCOL, GLYCERIN, SODIUM PCA, AMMONIUM LAURYL SULFATE, COCAMIDOPROPYL BETAINE, POLYQUATERNIUM-10, FRAGRANCE (PARFUM), DISODIUM PHOSPHATE, CETYL ALCOHOL, ALOE BARBADENSIS LEAF JUICE, CITRIC ACID, METHYLPARABEN, PROPYLPARABEN, RED 4 (CI 14700), YELLOW 5 (CI 19140).